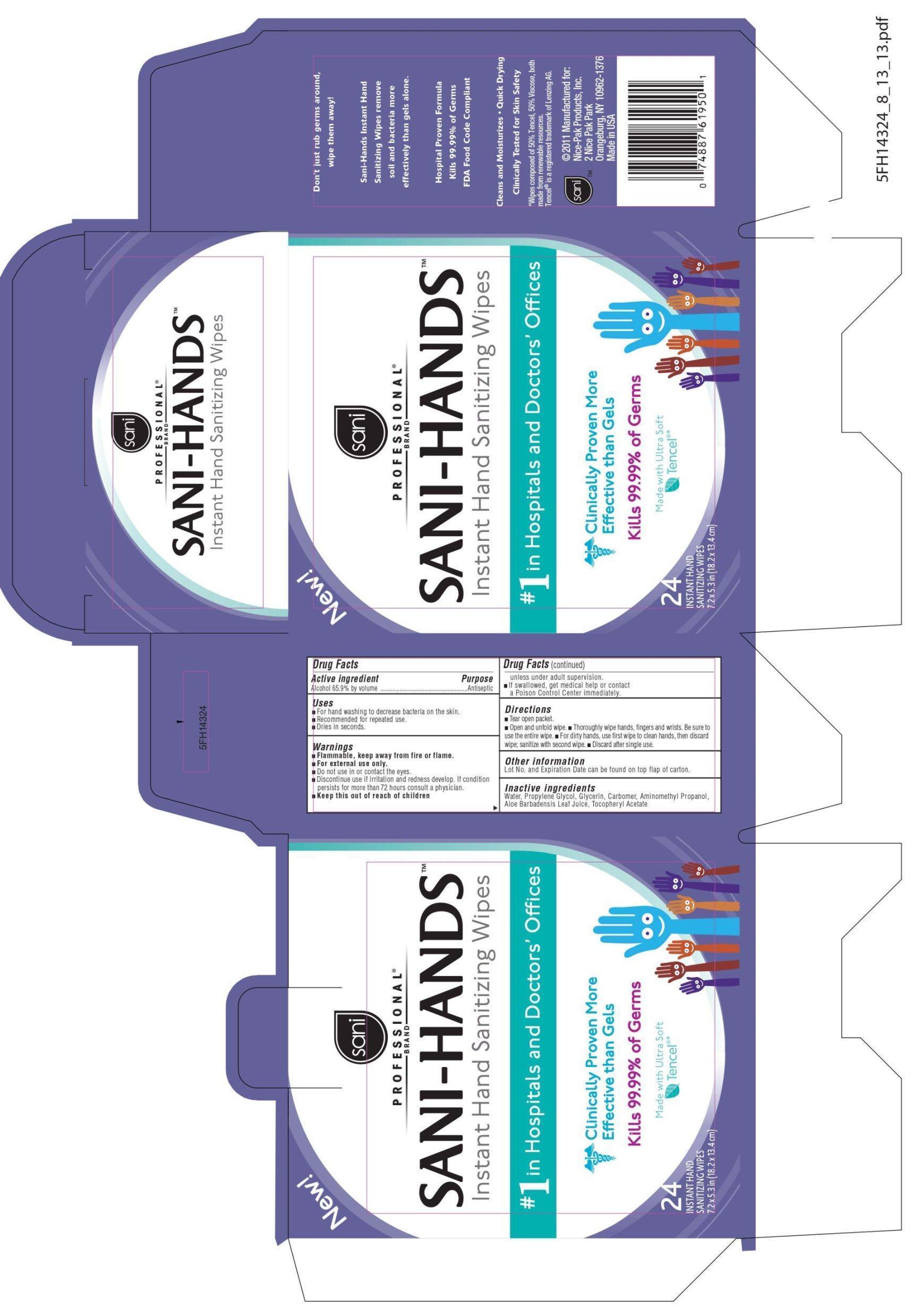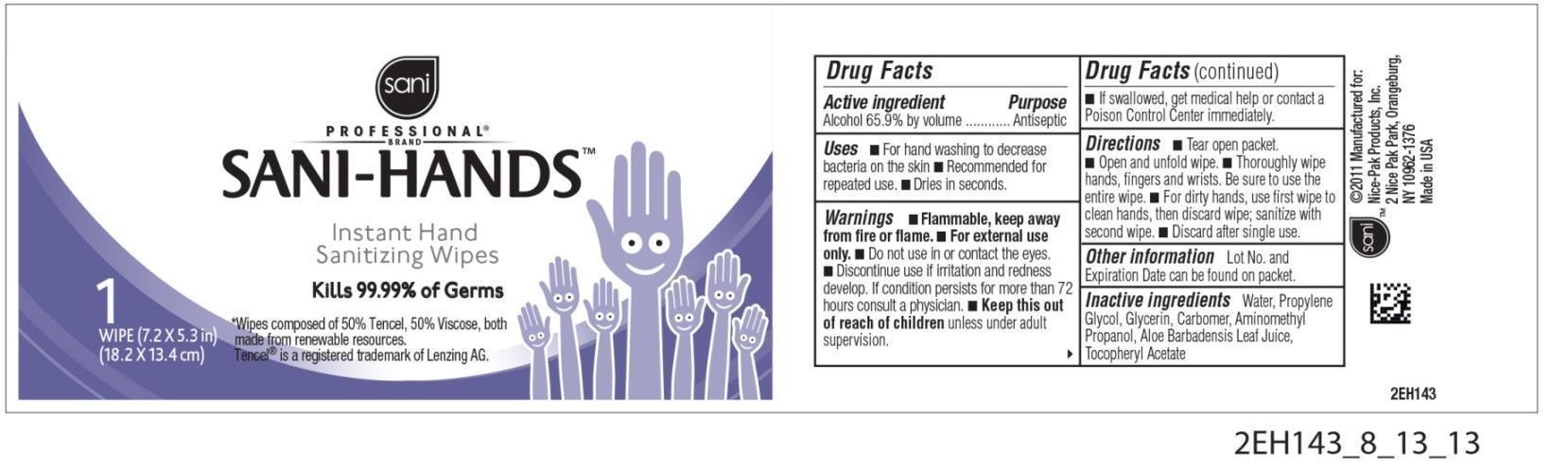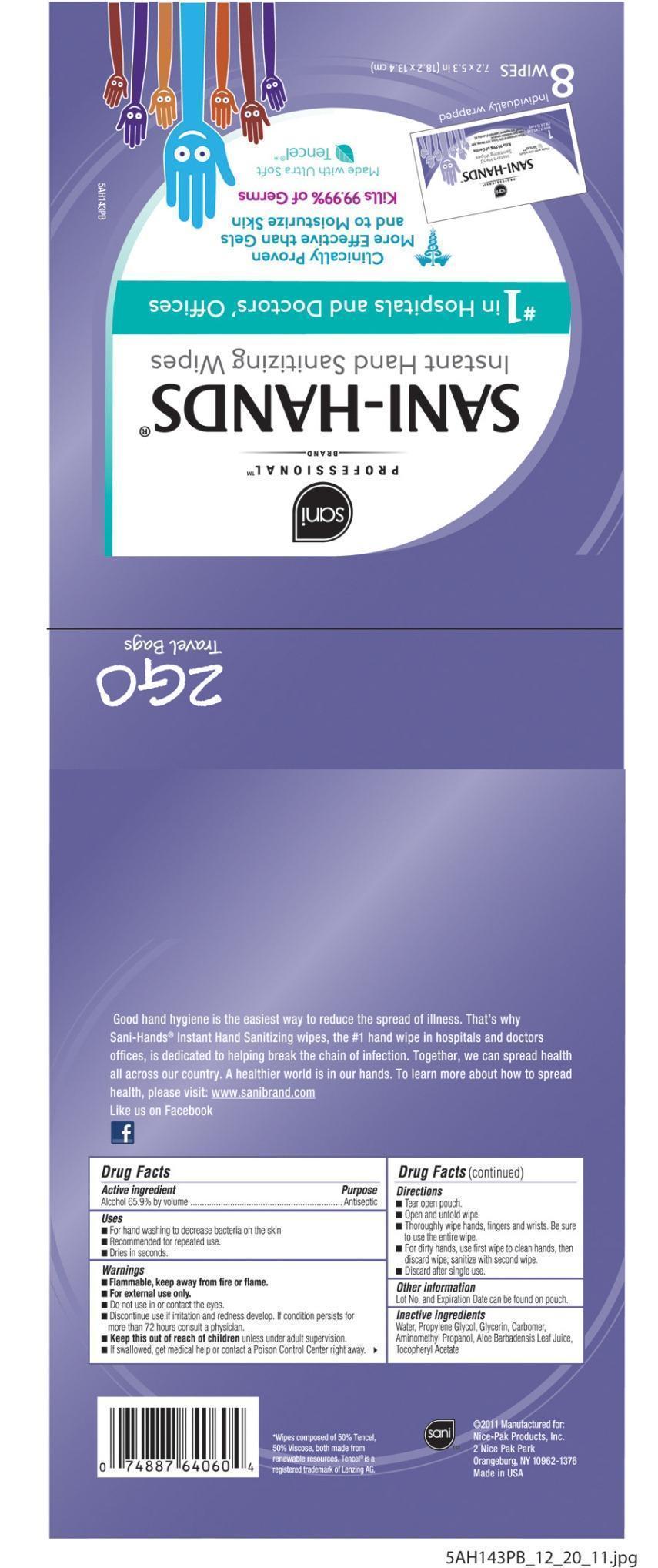 DRUG LABEL: Sani-Hands
NDC: 10819-5811 | Form: CLOTH
Manufacturer: Professional Disposables International, Inc.
Category: otc | Type: HUMAN OTC DRUG LABEL
Date: 20131128

ACTIVE INGREDIENTS: Alcohol 0.659 mL/1 1
INACTIVE INGREDIENTS: WATER; PROPYLENE GLYCOL; GLYCERIN; CARBOMER HOMOPOLYMER TYPE C; AMINOMETHYL PROPANEDIOL; ALOE VERA LEAF; ALPHA-TOCOPHEROL ACETATE

DRUG FACTS

Uses

- For hand washing to decrease bacteria on the skin.
- Recommended for repeated use.
- Dries in seconds.

Warnings

- Flammable, keep away from fire or flame.
- For external use only.
- Do not use in or contact the eyes.
- Discontinue use if irritation and redness develop. If condition persist for more than 72 hours consult a physician.
- If swallowed, get medical help or contact a Poison Control Center right away.

KEEP OUT OF REACH OF CHILDREN

- Keep this out of reach of children unless under adult supervision.

Directions

- Tear open pouch
- Open and unfold wipe.
- Thoroughly wipe hands, fingers and wrists. Be sure to utilize the entire wipe.
- For dirty hands, use first wipe to clean hands, then discard wipe; sanitize with second wipe.
- Discard after single use.

Other information

Lot No. and Expiration Date can be found on pouch, on packet or on top of carton.

Dosage

For dirty hand, use first wipe to clean hands, then discard wipe; sanitize with second wipe. Discard after single use.

Inactive ingredients

Water, Propylene Glycol, Glycerin, Carbomer, Aminometyl Propanol, Aloe Barbadensis Leaf Juice, Tocopheryl Acetate

*Wipes composed of 50% Tencel,
50% Viscose, both made from renewable resources.
Tencel(R) is a registered trademark of Lenzing AG.

Manufactured for:
Nice-Pak Products, Inc.
Orangeburg, NY 10962-1376 - USA - 1-800-999-6423
Made in USA

Principal Display Panel

Sani
Professional Brand
SANI-HANDS(R)
Instant Hand Sanitizing Wipes
#1 in Hospitals and Doctors' Offices
Clinically Proven More Effective than Gels

Kills 99.99% of Germs
Pouch Label
Individual packet
Box of 24 packets

Active ingredient

Alcohol 65.9% by volume

Purpose

Antiseptic